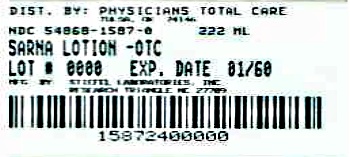 DRUG LABEL: Sarna
NDC: 54868-1587 | Form: LOTION
Manufacturer: Physicians Total Care, Inc.
Category: otc | Type: HUMAN OTC DRUG LABEL
Date: 20120911

ACTIVE INGREDIENTS: PRAMOXINE HYDROCHLORIDE 1 mg/1 mL
INACTIVE INGREDIENTS: BENZYL ALCOHOL; CARBOMER HOMOPOLYMER TYPE C; CETYL ALCOHOL; DIMETHICONE; GLYCERYL MONOSTEARATE; ISOPROPYL MYRISTATE; POLYOXYL 8 STEARATE; POLYOXYL 100 STEARATE; PETROLATUM; WATER; SODIUM HYDROXIDE; STEARIC ACID

Drug Facts

Active ingredient

Pramoxine hydrochloride 1%

Purpose

external analgesic

Use

for the temporary relief of itching associated with minor skin irritations

Warnings

For external use only

When using this product

- avoid contact with the eyes.

Stop use and ask a doctor if

- condition worsens
- symptoms persist for more than 7 days or clear up and occur again within a few days.

Caution -- Do not use in the eyes or nose. Not for prolonged use. Do not apply to large areas of the body. If redness, irritation, swelling, or pain persists or increases, discontinue use unless directed by a physician.

Keep out of reach of children.

If swallowed, get medical help or contact a Poison Control Center right away.

Directions

- To open, squeeze cap tightly and turn pump counter-clockwise.

Adults and children 2 years of age and older:

- apply to affected area not more than 3 to 4 times daily.

Children under 2 years of age: consult a doctor.

Other Information

Side effects may be reported to 1-888-438-7426

Inactive ingredients

benzyl alcohol, carbomer 940, cetyl alcohol, dimethicone, glyceryl stearate, isopropyl myristate, PEG-8 stearate, PEG-100 stearate, petrolatum, purified water, sodium hydroxide, stearic acid

Find more about Sarna!

Stiefel Laboratories, Inc.

Research Triangle Park, NC 27709

www.sarna-skincare.com

Made in Canada

A099718

Additional barcode labeling by:
Physicians Total Care, Inc.
Tulsa, Oklahoma 74146

Principal Display Panel

NDC 54868-1587-0

Sarna®

SENSITIVE

Pramoxine Hydrochloride 1%

ANTI-ITCH LOTION

Steroid-Free and Fragrance-Free

DERMATOLOGIST Recommended

- Relieves itching associated with:

DRY, SENSITIVE SKIN

ECZEMA

- Moisturizing

Net Wt. 7.5 Fl Oz. (222 mL)

A099717